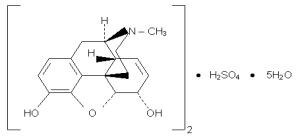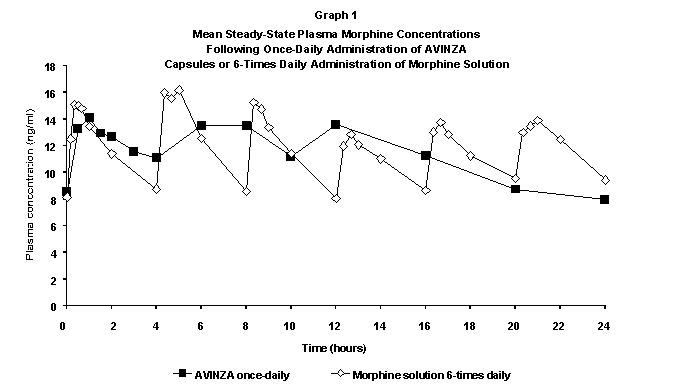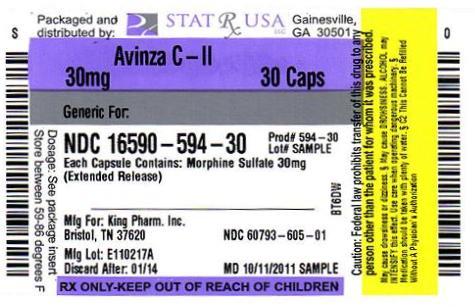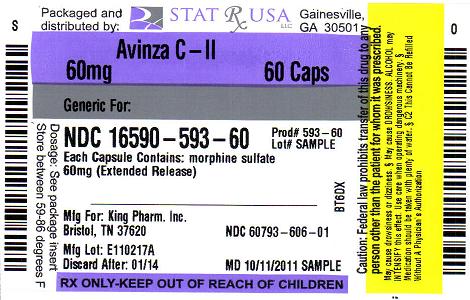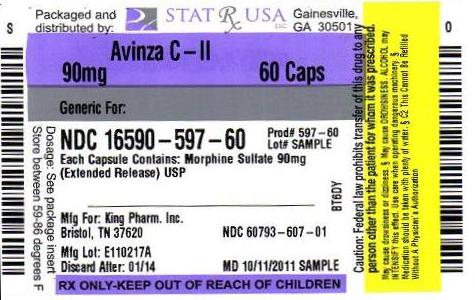 DRUG LABEL: AVINZA
NDC: 16590-594 | Form: CAPSULE, EXTENDED RELEASE
Manufacturer: STAT RX USA LLC
Category: prescription | Type: HUMAN PRESCRIPTION DRUG LABEL
Date: 20110922
DEA Schedule: CII

ACTIVE INGREDIENTS: MORPHINE SULFATE 30 mg/1 1
INACTIVE INGREDIENTS: FUMARIC ACID; POVIDONE; SODIUM LAURYL SULFATE; TALC; GELATIN; TITANIUM DIOXIDE; D&C YELLOW NO. 10

AVINZA® C II
(morphine sulfate extended-release capsules)
30 mg, 45 mg, 60 mg, 75 mg, 90 mg, 120 mg
Rx Only

WARNING:

AVINZA capsules are a modified-release formulation of morphine sulfate indicated for once daily administration for the relief of moderate to severe pain requiring continuous, around-the-clock opioid therapy for an extended period of time. AVINZA CAPSULES ARE TO BE SWALLOWED WHOLE OR THE CONTENTS OF THE CAPSULES SPRINKLED ON APPLESAUCE. THE CAPSULE BEADS ARE NOT TO BE CHEWED, CRUSHED, OR DISSOLVED DUE TO THE RISK OF RAPID RELEASE AND ABSORPTION OF A POTENTIALLY FATAL DOSE OF MORPHINE. PATIENTS MUST NOT CONSUME ALCOHOLIC BEVERAGES WHILE ON AVINZA THERAPY. ADDITIONALLY, PATIENTS MUST NOT USE PRESCRIPTION OR NON-PRESCRIPTION MEDICATIONS CONTAINING ALCOHOL WHILE ON AVINZA THERAPY. CONSUMPTION OF ALCOHOL WHILE TAKING AVINZA MAY RESULT IN THE RAPID RELEASE AND ABSORPTION OF A POTENTIALLY FATAL DOSE OF MORPHINE.

DESCRIPTION

AVINZA (morphine sulfate extended-release capsules) 30, 45, 60, 75, 90, and 120 mg contain both immediate release and extended release beads of morphine sulfate for once daily oral administration.

Chemically, morphine sulfate is 7,8-didehydro-4,5 alpha-epoxy-17-methylmorphinan-3,6 alpha-diol sulfate (2:1) (salt) pentahydrate with a molecular weight of 758. Morphine sulfate occurs as white, feathery, silky crystals; cubical masses of crystal; or white crystalline powder. It is soluble in water and slightly soluble in alcohol, but is practically insoluble in chloroform or ether. The octanol:water partition coefficient of morphine is 1.42 at physiologic pH and the pKa is 7.9 for the tertiary nitrogen (the majority is ionized at pH 7.4).

Each AVINZA Capsule contains either 30, 45, 60, 75, 90, or 120 mg of morphine sulfate, USP and the following inactive ingredients: ammoniomethacrylate copolymers, NF, fumaric acid, NF, povidone, USP, sodium lauryl sulfate, NF, sugar starch spheres, NF, and talc, USP. The capsule shell contains black ink, gelatin, titanium dioxide, D&C yellow No. 10 (30 mg), FD&C blue No. 2 (45 mg), FD&C green No. 3 (60 mg), FDA iron oxide and FDA yellow iron oxide (75 mg), FD&C red No. 40 (90 mg), FD&C red No. 3 (120 mg), and FD&C blue No. 1 (120 mg).

Structure:

AVINZA uses the proprietary SODAS® (Spheroidal Oral Drug Absorption System) technology to produce the extended release component of AVINZA, which combined with an immediate release component achieves the desired release profile characteristics of AVINZA capsules. Within the gastrointestinal tract, due to the permeability of the ammoniomethacrylate copolymers of the beads, fluid enters the beads and solubilizes the drug. This is mediated by fumaric acid, which acts as an osmotic agent and a local pH modifier. The resultant solution then diffuses out in a predetermined manner which prolongs the in vivo dissolution and absorption phases. (see Pharmacokinetics)

CLINICAL PHARMACOLOGY

Morphine, a pure opioid agonist, is relatively selective for the mu receptor, although it can interact with other opioid receptors at higher doses. In addition to analgesia, the widely diverse effects of morphine include drowsiness, changes in mood, respiratory depression, decreased gastrointestinal motility, nausea, vomiting, and alterations of the endocrine and autonomic nervous system.

Effects on the Central Nervous System (CNS): The principal therapeutic action of morphine is analgesia. Other therapeutic effects of morphine include anxiolysis, euphoria and feelings of relaxation. Although the precise mechanism of the analgesic action is unknown, specific CNS opiate receptors and endogenous compounds with morphine-like activity have been identified throughout the brain and spinal cord and are likely to play a role in the expression and perception of analgesic effects. In common with other opioids, morphine causes respiratory depression, in part by a direct effect on the brainstem respiratory centers. Morphine and related opioids depress the cough reflex by direct effect on the cough center in the medulla. Antitussive effects may occur with doses lower than those usually required for analgesia. Morphine causes miosis, even in total darkness. Pinpoint pupils are a sign of opioid overdose; however, when asphyxia is present during opioid overdose, marked mydriasis occurs.

Effects on the Gastrointestinal Tract and on Other Smooth Muscle: Gastric, biliary and pancreatic secretions are decreased by morphine. Morphine causes a reduction in motility and is associated with an increase in tone in the antrum of the stomach and duodenum. Digestion of food in the small intestine is delayed and propulsive contractions are decreased. Propulsive peristaltic waves in the colon are decreased, while tone is increased to the point of spasm. The end result may be constipation. Morphine can cause a marked increase in biliary tract pressure as a result of spasm of the sphincter of Oddi. Morphine may also cause spasm of the sphincter of the urinary bladder.

Effects on the Cardiovascular System: In therapeutic doses, morphine does not usually exert major effects on the cardiovascular system. Morphine produces peripheral vasodilation which may result in orthostatic hypotension and fainting. Release of histamine can occur, which may play a role in opioid-induced hypotension. Manifestations of histamine release and/or peripheral vasodilation may include pruritus, flushing, red eyes and sweating.

Pharmacodynamics

Morphine concentrations are not predictive of analgesic response, especially in patients previously treated with opioids. The minimum effective concentration varies widely and is influenced by a variety of factors, including the extent of previous opioid use, age, and general medical condition. Effective doses in tolerant patients may be significantly higher than in opioid-naïve patients.

In all patients, the dose of morphine should be titrated on the basis of clinical evaluation of the patient and to achieve a balance between therapeutic and adverse effects.

Pharmacokinetics

AVINZA consists of two components, an immediate release component that rapidly achieves plateau morphine plasma concentrations and an extended release component that maintains plasma concentrations throughout the 24-hour dosing interval. The amount of morphine absorbed from AVINZA following oral administration is similar to that absorbed from other oral morphine formulations.

The oral bioavailability of morphine is less than 40% and shows large inter-individual variability due to extensive pre-systemic metabolism.

Absorption

Following single-dose oral administration of a 60 mg dose of AVINZA under fasting conditions, morphine concentrations of approximately 3 to 6 ng/ml were achieved within 30 minutes after dosing and maintained for the 24-hour dosing interval. The pharmacokinetics of AVINZA were shown to be dose-proportional over a single oral dose range of 30 to 120 mg in healthy volunteers and a multiple oral dose range of at least 30 to 180 mg in patients with chronic moderate to severe pain.

Food Effects: When a 60 mg dose of AVINZA was administered immediately following a high fat meal, peak morphine concentrations and AUC values were similar to those observed when the dose of AVINZA was administered in a fasting state, although achievement of initial concentrations was delayed by approximately 1 hour under fed conditions. Therefore, AVINZA can be administered without regard to food. When the contents of AVINZA were administered by sprinkling on applesauce, the rate and extent of morphine absorption were found to be bioequivalent to the same dose when administered as an intact capsule.

Steady State: When dosed once-daily, AVINZA steady-state pharmacokinetics are characterized by a plateau-like plasma concentration profile. Steady-state plasma concentrations of morphine are achieved 2 to 3 days after initiation of once-daily administration of AVINZA.

AVINZA 60 mg Capsules (once-daily) and 10 mg morphine oral solution (6 times daily) were equally bioavailable.

A once-daily dose of AVINZA provided similar Cmax, Cmin, and AUC values and peak-trough fluctuations (% FL, Cmax-Cmin/Cav) compared to 6-times daily administration of the same total daily dose of morphine oral solution (Table 1).

Table 1 Pharmacokinetic Data Mean ± SD
Parameter | AVINZA Capsules Once-Daily | Morphine Oral Solution 6-Times Daily
AUC (ng/ml.h) | 273.25 ± 81.24 | 279.11 ± 63.00
Cmax (ng/ml) | 18.65 ± 7.13 | 19.96 ± 4.82
Cmin (ng/ml) | 6.98 ± 2.44 | 6.61 ±2.15
% FL | 106.38 ± 78.14 | 116.22 ±26.67

Distribution

Once absorbed, morphine is distributed to skeletal muscle, kidneys, liver, intestinal tract, lungs, spleen and brain. Although the primary site of action is the CNS, only small quantities cross the blood-brain barrier. Morphine also crosses the placental membranes and has been found in breast milk. The volume of distribution of morphine is approximately 1 to 6 L/kg, and morphine is 20 to 35% reversibly bound to plasma proteins.

Metabolism

The major pathway of morphine detoxification is conjugation, either with D-glucuronic acid to produce glucuronides or with sulfuric acid to produce morphine-3-etheral sulfate. While a small fraction (less than 5%) of morphine is demethylated, virtually all morphine is converted by hepatic metabolism to the 3- and 6-glucuronide metabolites (M3G and M6G; about 50% and 15%, respectively). M6G has been shown to have analgesic activity but crosses the blood-brain barrier poorly, while M3G has no significant analgesic activity.

Excretion

Most of a dose of morphine is excreted in urine as M3G and M6G, with elimination of morphine occurring primarily as renal excretion of M3G. Approximately 10% of the dose is excreted unchanged in urine. A small amount of the glucuronide conjugates are excreted in bile, with minor enterohepatic recycling. Seven to 10% of administered morphine is excreted in the feces.

The mean adult plasma clearance is approximately 20 to 30 ml/min/kg. The effective terminal half-life of morphine after IV administration is reported to be approximately 2 hours. In some studies involving longer periods of plasma sampling, a longer terminal half-life of morphine of about 15 hours was reported.

In Vitro AVINZA-Alcohol Interaction

In vitro studies performed by the FDA demonstrated that when AVINZA 30 mg was mixed with 900 mL of buffer solutions containing ethanol (20% and 40%), the dose of morphine that was released was alcohol concentration-dependent, leading to a more rapid release of morphine. While the relevance of in vitro lab tests regarding AVINZA to the clinical setting remains to be determined, this acceleration of release may correlate with in vivo rapid release of the total morphine dose, which could result in the absorption of a potentially fatal dose of morphine.

Special Populations

Geriatric: Elderly patients (aged 65 years or older) may have increased sensitivity to morphine. AVINZA pharmacokinetics have not been studied specifically in elderly patients.

Nursing Mothers: Low levels of morphine sulfate have been detected in maternal milk. The milk:plasma morphine AUC ratio is about 2.5:1. The amount of morphine delivered to the infant depends on the plasma concentration of the mother, the amount of milk ingested by the infant, and the extent of first-pass metabolism.

Pediatric: The pharmacokinetics of AVINZA have not been studied in pediatric patients below the age of 18. The range of dose strengths available may not be appropriate for treatment of very young pediatric patients. Sprinkling on applesauce is NOT a suitable alternative for these patients.

Gender: A gender analysis of pharmacokinetic data from healthy subjects taking AVINZA indicated that morphine concentrations were similar in males and females.

Race: There may be some pharmacokinetic differences associated with race. In one published study, Chinese subjects given intravenous morphine had a higher clearance when compared to Caucasian subjects (1852 +/- 116 ml/min compared to 1495 +/- 80 ml/min).

Hepatic Failure: Morphine pharmacokinetics have been reported to be significantly altered in patients with cirrhosis. Clearance was found to decrease with a corresponding increase in half-life. The M3G and M6G to morphine plasma AUC ratios also decreased in these subjects, indicating diminished metabolic activity.

Renal Insufficiency: Morphine pharmacokinetics are altered in patients with renal failure. Clearance is decreased and the metabolites, M3G and M6G, may accumulate to much higher plasma levels in patients with renal failure as compared to patients with normal renal function.

Drug-Drug Interactions: Known drug-drug interactions involving morphine are pharmacodynamic, not pharmacokinetic. (see PRECAUTIONS, Drug Interactions)

Clinical Studies

AVINZA was studied in over 140 healthy volunteers and 560 patients with chronic, moderate to severe pain who participated in 6 pharmacokinetic studies, 4 clinical studies and 3 studies which provided both pharmacokinetic and clinical data. The patient population included those who were either receiving chronic opioid therapy or had a prior sub-optimal response to acetaminophen and/or NSAID therapy, as well as patients who previously received intermittent opioid analgesic therapy. In the controlled clinical studies, patients were followed from 7 days to up to 4 weeks, and in the open label studies, patients were followed for up to 6 to 12 months.

AVINZA was studied in a double-blind, placebo-controlled, fixed-dose, parallel group trial in 295 patients with moderate to severe pain due to osteoarthritis. These patients had either a prior sub-optimal response to acetaminophen, NSAID therapy, or previously received intermittent opioid analgesic therapy. Thirty-milligrams AVINZA capsules administered once-daily, either in the morning or the evening, were more effective than placebo in reducing pain.

Table 2 Change from Baseline in WOMAC OA Index Pain VAS Subscale Score
Overall | Placebo | AVINZA QAM | AVINZA QPM
LS Mean | -36.23 | -75.26 [P<0.05; REPEATED MEASURES ANALYSIS] | -75.39
Std. Error | 11.482 | 11.305 | 11.747

This study was not designed to assess the effects of AVINZA on the course of the osteoarthritis.

INDICATIONS AND USAGE

AVINZA capsules are a modified-release formulation of morphine sulfate intended for once daily administration indicated for the relief of moderate to severe pain requiring continuous, around-the-clock opioid therapy for an extended period of time.

AVINZA is NOT intended for use as a prn analgesic.

The safety and efficacy of using AVINZA in the postoperative setting has not been evaluated. AVINZA is not indicated for postoperative use. If the patient has been receiving the drug prior to surgery, resumption of the pre-surgical dose may be appropriate once the patient is able to take the drug by mouth. Physicians should individualize treatment, moving from parenteral to oral analgesics as appropriate. (see American Pain Society guidelines)

CONTRAINDICATIONS

AVINZA is contraindicated in patients with known hypersensitivity to morphine, morphine salts, or any components of the product. AVINZA, like all opioids, is contraindicated in patients with respiratory depression in the absence of resuscitative equipment and in patients with acute or severe bronchial asthma.

AVINZA, like all opioids, is contraindicated in any patient who has or is suspected of having paralytic ileus.

WARNINGS

AVINZA must be swallowed whole (not chewed, crushed, or dissolved) or AVINZA may be opened and the entire bead contents sprinkled on a small amount of applesauce immediately prior to ingestion. THE CAPSULES MUST NOT BE CHEWED, CRUSHED, OR DISSOLVED DUE TO THE RISK OF RAPID RELEASE AND ABSORPTION OF A POTENTIALLY FATAL DOSE OF MORPHINE. (see BOX WARNING, CLINICAL PHARMACOLOGY)

Patients must not consume alcoholic beverages while on AVINZA therapy. Additionally, patients must not use prescription or non-prescription medications containing alcohol while on AVINZA therapy. Consumption of alcohol while taking AVINZA may result in the rapid release and absorption of a potentially fatal dose of morphine.

THE DAILY DOSE OF AVINZA MUST BE LIMITED TO A MAXIMUM OF 1600 MG/DAY. AVINZA DOSES OF OVER 1600 MG/DAY CONTAIN A QUANTITY OF FUMARIC ACID THAT HAS NOT BEEN DEMONSTRATED TO BE SAFE, AND WHICH MAY RESULT IN SERIOUS RENAL TOXICITY.

Misuse, Abuse and Diversion of Opioids

Morphine is an opioid agonist and a Schedule II controlled substance. Such drugs are sought by drug abusers and people with addiction disorders. Diversion of Schedule II products is an act subject to criminal penalty.

Morphine can be abused in a manner similar to other opioid agonists, legal or illicit. This should be considered when prescribing or dispensing AVINZA in situations where the physician or pharmacist is concerned about an increased risk of misuse, abuse, or diversion.

Abuse of AVINZA by crushing, chewing, snorting, or injecting the dissolved product will result in the immediate release of the entire daily dose of the opioid and pose a significant risk to the abuser that could result in overdose and death. Intravenous abuse of a water extract of AVINZA may lead to serious pulmonary complications due to the extraction of talc along with morphine sulfate. (see DRUG ABUSE AND ADDICTION)

Concerns about abuse, addiction, and diversion should not prevent the proper management of pain. Healthcare professionals should contact their State Professional Licensing Board, or State Controlled Substances Authority for information on how to prevent and detect abuse or diversion of this product.

Interactions with Alcohol and Drugs of Abuse

Morphine may be expected to have additive effects when used in conjunction with alcohol, other opioids, or illicit drugs that cause central nervous system depression. In vitro studies performed by the FDA demonstrated that when AVINZA 30 mg was mixed with 900 mL of buffer solutions containing ethanol (20% and 40%), the dose of morphine that was released was alcohol concentration-dependent, leading to a more rapid release of morphine. While the relevance of in vitro lab tests regarding AVINZA to the clinical setting remains to be determined, this acceleration of release may correlate with in vivo rapid release of the total morphine dose, which could result in the absorption of a potentially fatal dose of morphine.

Impaired Respiration

Respiratory depression is the chief hazard of all morphine preparations. Respiratory depression occurs more frequently in elderly or debilitated patients and in those suffering from conditions accompanied by hypoxia, hypercapnia, or upper airway obstruction, in whom even moderate therapeutic doses may significantly decrease pulmonary ventilation.

Morphine should be used with extreme caution in patients with chronic obstructive pulmonary disease or cor pulmonale and in patients having a substantially decreased respiratory reserve (e.g., severe kyphoscoliosis), hypoxia, hypercapnia, or pre-existing respiratory depression. In such patients, even usual therapeutic doses of morphine may increase airway resistance and decrease respiratory drive to the point of apnea.

Head Injury and Increased Intracranial Pressure

The respiratory depressant effects of morphine with carbon dioxide retention and secondary elevation of cerebrospinal fluid pressure may be markedly exaggerated in the presence of head injury, other intracranial lesions, or a pre-existing increase in intracranial pressure. Morphine produces effects which may obscure neurologic signs of further increases in intracranial pressure in patients with head injuries. Morphine should only be administered under such circumstances when considered essential and then with extreme care.

Hypotensive Effect

AVINZA, like all morphine products, may cause severe hypotension in an individual whose ability to maintain blood pressure has already been compromised by a depleted blood volume or concurrent administration of drugs such as phenothiazines or general anesthetics. (see also PRECAUTIONS, Drug Interactions) AVINZA may produce orthostatic hypotension and syncope in ambulatory patients.

AVINZA is an opioid analgesic which should be administered with caution to patients in circulatory shock, as vasodilation produced by the drug may further reduce cardiac output and blood pressure.

Gastrointestinal Obstruction

AVINZA should not be administered to patients with gastrointestinal obstruction, especially paralytic ileus because AVINZA, like all morphine preparations, diminishes propulsive peristaltic waves in the gastrointestinal tract and may prolong the obstruction.

PRECAUTIONS

General

AVINZA is intended for use in patients requiring continuous around-the-clock treatment with an opioid analgesic. It is not appropriate as a prn treatment for pain. As with any opioid, it is critical to adjust the dose of AVINZA for each individual patient, taking into account the patient’s prior experience with analgesics. (see DOSAGE AND ADMINISTRATION)

Use in Pancreatic/Biliary Tract Disease

AVINZA should be used with caution in patients with biliary tract disease, including acute pancreatitis, as morphine may cause spasm of the sphincter of Oddi and diminish biliary and pancreatic secretions.

Special Risk Groups

AVINZA should be administered cautiously and in reduced dosages in patients with severe renal or hepatic insufficiency, Addison's disease, hypothyroidism, prostatic hypertrophy, or urethral stricture, and in elderly or debilitated patients. (see Geriatric Use and CLINICAL PHARMACOLOGY, Special Populations)

Caution should be exercised in the administration of morphine to patients with CNS depression, toxic psychosis, acute alcoholism and delirium tremens, and seizure disorders.

Driving and Operating Machinery

Patients should be cautioned that AVINZA could impair the mental and/or physical abilities needed to perform potentially hazardous activities such as driving a car or operating machinery.

Patients should also be cautioned about the potential combined effects of AVINZA with other CNS depressants, including other opioids, phenothiazines, sedative/hypnotics and alcohol. (see PRECAUTIONS, Drug Interactions)

Tolerance and Physical Dependence

Tolerance is the need for increasing doses of opioids to maintain a defined effect such as analgesia (in the absence of disease progression or other external factors). Physical dependence is manifested by withdrawal symptoms after abrupt discontinuation of a drug or upon administration of an antagonist. Physical dependence and tolerance are not unusual during chronic opioid therapy.

The opioid abstinence or withdrawal syndrome is characterized by some or all of the following: restlessness, lacrimation, rhinorrhea, yawning, perspiration, chills, myalgia, and mydriasis. Other symptoms also may develop, including irritability, anxiety, backache, joint pain, weakness, abdominal cramps, insomnia, nausea, anorexia, vomiting, diarrhea, or increased blood pressure, respiratory rate, or heart rate.

In general, opioids should not be abruptly discontinued. (see DOSAGE AND ADMINISTRATION, Cessation of Therapy)

Information for Patients

Patients receiving AVINZA (morphine sulfate extended-release capsules) should be given the following instructions by the physician:

1. Patients should be advised that AVINZA capsules contain morphine and should be taken once daily.
2. AVINZA must be swallowed whole (not chewed, crushed, or dissolved) or AVINZA may be opened and the entire bead contents sprinkled on a small amount of applesauce immediately prior to ingestion. The beads must NOT be chewed, crushed, or dissolved due to the risk of exposure to a potentially toxic dose of morphine.
3. Patients should be informed that they must not consume alcoholic beverages while on AVINZA therapy. Additionally, patients should be informed that they must not use prescription or non-prescription medication containing alcohol while on AVINZA therapy. Consumption of alcohol while taking AVINZA may result in the rapid release and absorption of a potentially fatal dose of morphine.
4. The dose of AVINZA should not be adjusted without consulting with a physician or other healthcare professional.
5. Patients should be advised that AVINZA may impair mental and/or physical ability required for the performance of potentially hazardous tasks (e.g., driving, operating machinery). Patients started on AVINZA or patients whose dose has been adjusted should refrain from any potentially dangerous activity until it is established that they are not adversely affected.
6. Patients should be advised that AVINZA should not be combined with alcohol or other CNS depressants (e.g., sleep medications, tranquilizers). A physician should be consulted if other medications are currently being used or are added in the future.
7. Women of childbearing potential who become or are planning to become pregnant should consult a physician prior to initiating or continuing therapy with AVINZA.
8. If patients have been receiving treatment with AVINZA for more than a few weeks and cessation of therapy is indicated, they should be counseled on the importance of safely tapering the dose and that abruptly discontinuing the medication could precipitate withdrawal symptoms. The physician should provide a dose schedule to accomplish a gradual discontinuation of the medication.
9. Patients should be advised that AVINZA is a potential drug of abuse. They should protect it from theft. It should never be given to anyone other than the individual for whom it was prescribed.
10. Patients should be instructed to keep AVINZA in a secure place out of the reach of children. When AVINZA is no longer needed, the unused capsules should be destroyed by flushing down the toilet.

As with other opioids, patients taking AVINZA should be advised of the potential for severe constipation; appropriate laxatives, and/or stool softeners as well as other appropriate treatments should be initiated from the onset of opioid therapy.

Drug Interactions

CNS Depressants: The concurrent use of other central nervous system (CNS) depressants including sedatives, hypnotics, general anesthetics, antiemetics, phenothiazines, or other tranquilizers or alcohol increases the risk of respiratory depression, hypotension, profound sedation, or coma. Use with caution and in reduced dosages in patients taking these agents.

Muscle Relaxants: Morphine may enhance the neuromuscular blocking action of skeletal muscle relaxants and produce an increased degree of respiratory depression.

Mixed Agonist/Antagonist Opioid Analgesics: Mixed agonist/antagonist analgesics (i.e., pentazocine, nalbuphine and butorphanol) should NOT be administered to patients who have received or are receiving a course of therapy with a pure opioid agonist analgesic. In these patients, mixed agonist/antagonist analgesics may reduce the analgesic effect and/or may precipitate withdrawal symptoms.

Monoamine Oxidase Inhibitors (MAOIs): MAOIs markedly potentiate the action of morphine. AVINZA should not be used in patients taking MAOIs or within 14 days of stopping such treatment.

Cimetidine: Concomitant administration of morphine and cimetidine has been reported to precipitate apnea, confusion and muscle twitching in an isolated report. Patients should be monitored for increased respiratory and CNS depression when receiving cimetidine concomitantly with AVINZA.

Food: AVINZA can be administered without regard to food. (see CLINICAL PHARMACOLOGY, Food Effects).

Carcinogenicity/Mutagenicity/Impairment of Fertility

Studies in animals to evaluate the carcinogenic potential of morphine sulfate have not been conducted. No formal studies to assess the mutagenic potential of morphine have been conducted. In the published literature, the results of in vitro studies showed that morphine is non-mutagenic in the Drosophila melanogaster lethal mutation assay and produced no evidence of chromosomal aberrations when incubated with murine splenocytes. Contrary to these results, morphine was found to increase DNA fragmentation when incubated in vitro with a human lymphoma cell line. In vivo, morphine has been reported to produce an increase in the frequency of micronuclei in bone marrow cells and immature red blood cells in the mouse micronucleus test and to induce chromosomal aberrations in murine lymphocytes and spermatids. Some of the in vivo clastogenic effects reported with morphine in mice may be directly related to increases in glucocorticoid levels produced by morphine in this species.

Pregnancy

Teratogenic Effects (Pregnancy Category C)

No formal studies to assess the teratogenic effects of morphine in animals have been performed. Several literature reports indicate that morphine administered subcutaneously during the early gestational period in mice and hamsters produced neurological, soft tissue and skeletal abnormalities. With one exception, the effects that have been reported were following doses that were maternally toxic and the abnormalities noted were characteristic of those observed when maternal toxicity is present. In one study, following subcutaneous infusion of doses greater than or equal to 0.15 mg/kg to mice, exencephaly, hydronephrosis, intestinal hemorrhage, split supraoccipital, malformed sternebrae, and malformed xiphoid were noted in the absence of maternal toxicity. In the hamster, morphine sulfate given subcutaneously on gestation day 8 produced exencephaly and cranioschisis. Morphine was not a significant teratogen in the rat at exposure levels significantly beyond that normally encountered in clinical practice. In one study however, decreased litter size and viability were observed in the offspring of male rats administered morphine at doses approximately 3-fold the maximum recommended human daily dose (MRHDD) for 10 days prior to mating. In two studies performed in the rabbit, no evidence of teratogenicity was reported at subcutaneous doses up to 100 mg/kg.

In humans, the frequency of congenital anomalies has been reported to be no greater than expected among the children of 70 women who were treated with morphine during the first four months of pregnancy or in 448 women treated with this drug anytime during pregnancy. Furthermore, no malformations were observed in the infant of a woman who attempted suicide by taking an overdose of morphine and other medication during the first trimester of pregnancy.

Nonteratogenic Effects

Published literature has reported that exposure to morphine during pregnancy is associated with reduction in growth and a host of behavioral abnormalities in the offspring of animals. Morphine treatment during gestational periods of organogenesis in rats, hamsters, guinea pigs and rabbits resulted in the following treatment-related embryotoxicity and neonatal toxicity in one or more studies: decreased litter size, embryo-fetal viability, fetal and neonatal body weights, absolute brain and cerebellar weights, lengths or widths at birth and during the neonatal period, delayed motor and sexual maturation, and increased neonatal mortality, cyanosis and hypothermia. Decreased fertility in female offspring, and decreased plasma and testicular levels of luteinizing hormone and testosterone, decreased testes weights, seminiferous tubule shrinkage, germinal cell aplasia, and decreased spermatogenesis in male offspring were also observed. Behavioral abnormalities resulting from chronic morphine exposure of fetal animals included altered reflex and motor skill development, mild withdrawal, and altered responsiveness to morphine persisting into adulthood.

Controlled studies of chronic in utero morphine exposure in pregnant women have not been conducted. Infants born to mothers who have taken opioids chronically may exhibit withdrawal symptoms, reversible reduction in brain volume, small size, decreased ventilatory response to CO2 and increased risk of sudden infant death syndrome. Morphine sulfate should be used by a pregnant woman only if the need for opioid analgesia clearly outweighs the potential risks to the fetus.

Labor and Delivery

Opioids cross the placenta and may produce respiratory depression and psycho-physiologic effects in neonates. AVINZA is not recommended for use in women during and immediately prior to labor, when use of shorter acting analgesics or other analgesic techniques are more appropriate. Occasionally, opioid analgesics may prolong labor through actions which temporarily reduce the strength, duration and frequency of uterine contractions. However this effect is not consistent and may be offset by an increased rate of cervical dilatation, which tends to shorten labor. Neonates whose mothers received opioid analgesics during labor should be observed closely for signs of respiratory depression. A specific opioid antagonist, such as naloxone or nalmefene, should be available for reversal of opioid-induced respiratory depression in the neonate.

Neonatal Withdrawal Syndrome

Chronic maternal use of opioids during pregnancy may cause newborns to suffer from neonatal withdrawal syndrome (NWS) following birth. Manifestations of this syndrome include irritability, hyperactivity, abnormal sleep pattern, high-pitched cry, tremor, vomiting, diarrhea, weight loss, and failure to gain weight. The time and amount of the mother’s last dose, and the rate of elimination of the drug from the newborn may affect the onset, duration, and severity of the disorder. When severe symptoms occur, pharmacologic intervention may be required.

Nursing Mothers

Low levels of morphine sulfate have been detected in human milk. Breast-feeding infants might experience withdrawal symptoms upon cessation of AVINZA administration to the mother. Because of the potential for nursing infants to experience adverse reactions, a decision should be made whether to discontinue nursing or discontinue AVINZA, taking into account the benefit of the drug to the mother.

Pediatric Use

Safety and effectiveness of AVINZA in pediatric patients below the age of 18 have not been established. The range of dose strengths available may not be appropriate for treatment of very young pediatric patients. Sprinkling on applesauce is NOT a suitable alternative for these patients.

Geriatric Use

Of the total number of subjects in clinical studies of AVINZA, there were 168 patients age 65 and over, including 64 patients over the age of 74, 100 of whom were treated with AVINZA. Subgroup analyses comparing efficacy were not possible given the small number of subjects in each treatment group. No overall differences in safety were observed between these subjects and younger subjects. In general, caution should be exercised in the selection of the starting dose of AVINZA for an elderly patient, usually starting at the low end of the dosing range. As with all opioids, the starting dose should be reduced in debilitated and non-tolerant patients. (see CLINICAL PHARMACOLOGY, Special Populations, Geriatric, and PRECAUTIONS, Special Risk Groups)

ADVERSE REACTIONS

In controlled and open label clinical studies, 560 patients with chronic malignant or non-malignant pain were treated with AVINZA. The most common serious adverse events reported with administration of AVINZA were vomiting, nausea, death, dehydration, dyspnea, and sepsis. (Deaths occurred in patients treated for pain due to underlying malignancy.) Serious adverse events caused by morphine include respiratory depression, apnea, and to a lesser degree, circulatory depression, respiratory arrest, shock and cardiac arrest.

Adverse Events

The common adverse events seen on initiation of therapy with morphine are dose-dependent and are typical opioid-related side effects. The most frequent of these include constipation, nausea and somnolence. The frequency of these events depends upon several factors including the clinical setting, the patient’s level of opioid tolerance, and host factors specific to the individual. These events should be anticipated and managed as part of opioid analgesia therapy.

The most common adverse events (seen in greater than 10%) reported by patients treated with AVINZA during the clinical trials at least once during therapy were constipation, nausea, somnolence, vomiting, and headache. Adverse events occurring in 5-10% of study patients were peripheral edema, diarrhea, abdominal pain, infection, urinary tract infection, accidental injury, flu syndrome, back pain, rash, sweating, fever, insomnia, depression, paresthesia, anorexia, dry mouth, asthenia and dyspnea. Other less common side effects expected from opioid analgesics, including morphine, or seen in fewer than 5% of patients taking AVINZA in the clinical trials were:

Body as a Whole: malaise, withdrawal syndrome.

Cardiovascular System: bradycardia, hypertension, hypotension, palpitations, syncope, tachycardia.

Digestive System: biliary pain, dyspepsia, dysphagia, gastroenteritis, abnormal liver function tests, rectal disorder, thirst.

Hemic and Lymphatic System: anemia, thrombocytopenia.

Metabolic and Nutritional Disorders: edema, weight loss.

Musculoskeletal: skeletal muscle rigidity.

Nervous System: abnormal dreams, abnormal gait, agitation, amnesia, anxiety, ataxia, confusion, convulsions, coma, delirium, euphoria, hallucinations, lethargy, nervousness, abnormal thinking, tremor, vasodilation, vertigo.

Respiratory System: hiccup, hypoventilation, voice alteration.

Skin and Appendages: dry skin, urticaria.

Special Senses: amblyopia, eye pain, taste perversion.

Urogenital System: abnormal ejaculation, dysuria, impotence, decreased libido, oliguria, urinary retention.

DRUG ABUSE AND ADDICTION

AVINZA is a mu-agonist opioid and is a Schedule II controlled substance. Morphine, like other opioids used in analgesia, can be abused and is subject to criminal diversion.

Drug addiction is characterized by compulsive use, use for non-medical purposes, and continued use despite harm or risk of harm. Drug addiction is a treatable disease, utilizing a multi-disciplinary approach, but relapse is common.

“Drug-seeking” behavior is very common in addicts and drug abusers. Drug-seeking tactics include emergency calls or visits near the end of office hours, refusal to undergo appropriate examination, testing or referral, repeated “loss” of prescriptions, tampering with prescriptions and reluctance to provide prior medical records or contact information for other treating physician(s). “Doctor shopping” to obtain additional prescriptions is common among drug abusers and people suffering from untreated addiction.

Abuse and addiction are separate and distinct from physical dependence and tolerance. Physicians should be aware that addiction may not be accompanied by concurrent tolerance and symptoms of physical dependence. The converse is also true. In addition, abuse of opioids can occur in the absence of true addiction and is characterized by misuse for non-medical purposes, often in combination with other psychoactive substances. Careful record-keeping of prescribing information, including quantity, frequency, and renewal requests is strongly advised.

Proper assessment of the patient, proper prescribing practices, periodic re-evaluation of therapy, and proper dispensing and storage are appropriate measures that help to limit abuse of opioid drugs.

AVINZA is intended for oral use only. Abuse of the crushed capsule poses a hazard of overdose and death. This risk is increased with concurrent abuse of alcohol and other substances. With parenteral abuse, the capsule excipients, especially talc, can be expected to result in local tissue necrosis, infection, pulmonary granulomas, and increased risk of endocarditis and valvular heart injury. Parenteral drug abuse is commonly associated with transmission of infectious diseases such as hepatitis and HIV.

AVINZA OVERDOSAGE

Symptoms

Acute overdosage with morphine is manifested by respiratory depression, somnolence progressing to stupor or coma, skeletal muscle flaccidity, cold and clammy skin, constricted pupils, and, in some cases, pulmonary edema, bradycardia, hypotension, and death.

Treatment

Primary attention should be given to re-establishment of a patent airway and institution of assisted or controlled ventilation when overdose of an extended-release formulation such as AVINZA has been ingested. Elimination or evacuation of gastric contents may be necessary in order to eliminate unabsorbed drug. Before attempting treatment by gastric emptying or activated charcoal, care should be taken to secure the airway. Pure opioid antagonists, naloxone or nalmefene, are specific antidotes to respiratory depression resulting from opioid overdose. Since the duration of reversal is expected to be less than the duration of action of AVINZA, the patient must be carefully monitored until spontaneous respiration is reliably re-established. AVINZA, as with other controlled delivery preparations in overdose situations, may continue to release morphine for 36 to 48 hours or longer following ingestion, and management of an overdose should be monitored accordingly. If the response to opioid antagonists is suboptimal or only brief in nature, additional antagonist should be administered as directed by the manufacturer of the product.

Opioid antagonists should not be administered in the absence of clinically significant respiratory or circulatory depression secondary to morphine overdose. Such agents should be administered cautiously to persons who are known, or suspected to be physically dependent on AVINZA. In such cases, an abrupt or complete reversal of opioid effects may precipitate an acute abstinence syndrome.

Opioid-Tolerant Individuals: In an individual physically dependent on opioids, administration of the usual dose of the antagonist will precipitate an acute withdrawal syndrome. The severity of the withdrawal symptoms experienced will depend on the degree of physical dependence and the dose of the antagonist administered. Use of an opioid antagonist should be reserved for cases where such treatment is clearly needed. If it is necessary to treat serious respiratory depression in the physically dependent patient, administration of the antagonist should be initiated with care and titrated with smaller than usual doses.

Supportive measures (including oxygen, vasopressors) should be employed in the management of circulatory shock and pulmonary edema as indicated. Cardiac arrest or arrhythmias may require cardiac massage or defibrillation.

DOSAGE AND ADMINISTRATION

AVINZA MUST BE SWALLOWED WHOLE (NOT CHEWED, CRUSHED, OR DISSOLVED) OR AVINZA MAY BE OPENED AND THE ENTIRE BEAD CONTENTS SPRINKLED ON A SMALL AMOUNT OF APPLESAUCE IMMEDIATELY PRIOR TO INGESTION. THE BEADS MUST NOT BE CHEWED, CRUSHED, OR DISSOLVED DUE TO RISK OF ACUTE OVERDOSE. INGESTING CHEWED OR CRUSHED AVINZA BEADS WILL LEAD TO THE RAPID RELEASE AND ABSORPTION OF A POTENTIALLY TOXIC DOSE OF MORPHINE.

Patients must not consume alcoholic beverages while on AVINZA therapy. Additionally, patients must not use prescription or non-prescription medicine containing alcohol while on AVINZA therapy. Consumption of alcohol while taking AVINZA may result in the rapid release and absorption of a potentially fatal dose of morphine.

The daily dose of AVINZA must be limited to a maximum of 1600 mg/day. AVINZA doses of over 1600 mg/day contain a quantity of fumaric acid that has not been demonstrated to be safe, and which may result in serious renal toxicity. (see WARNINGS)

The 45, 60, 75, 90, and 120 mg capsules are for use only in opioid-tolerant patients.

All doses are intended to be administered once daily. As with any opioid drug product, it is necessary to adjust the dosing regimen for each patient individually, taking into account the patient's prior analgesic treatment experience. In the selection of the initial dose of AVINZA, attention should be given to the following:

1. the total daily dose, potency and specific characteristics of the opioid the patient has been taking previously;
2. the reliability of the relative potency estimate used to calculate the equivalent morphine dose needed;
3. the patient’s degree of opioid tolerance;
4. the general condition and medical status of the patient;
5. concurrent medications;
6. the type and severity of the patient's pain.

The following dosing recommendations, therefore, can only be considered suggested approaches to what is actually a series of clinical decisions over time in the management of the pain of each individual patient.

Conversion from Other Oral Morphine Formulations to AVINZA

Patients receiving other oral morphine formulations may be converted to AVINZA by administering the patient's total daily oral morphine dose as AVINZA once-daily. AVINZA should not be given more frequently than every 24 hours. As with conversion from any oral morphine formulation to another, supplemental pain medication may be required until the response to the patient's daily AVINZA dosage has stabilized (up to 4 days).

Conversion from Parenteral Morphine or Other Non-Morphine Opioids (Parenteral or Oral) to AVINZA

There is inter-patient variability in the potency of opioid drugs and opioid formulations. Therefore, a conservative approach is advised when determining the total daily dose of AVINZA. It is better to underestimate a patient’s 24-hour oral morphine dose and make available rescue medication than to overestimate the 24-hour oral morphine dose and manage an adverse experience or overdose. The following general points should be considered regarding opioid conversions.

Parenteral to oral morphine ratio: Anywhere from 3 to 6 mg of oral morphine may be required to provide pain relief equivalent to 1 mg of parenteral morphine. Based on this rationale, a reasonable starting dose of AVINZA would be approximately three times the previous daily parenteral morphine requirement.

Other parenteral or oral non-morphine opioids to oral morphine sulfate: Physicians and other healthcare professionals are advised to refer to published relative potency information, keeping in mind that conversion ratios are only approximate. In general, it is safest to administer half of the estimated daily morphine requirement as the initial AVINZA dose once per day and then manage insufficient pain relief by supplementation with immediate-release morphine or other short-acting analgesics. (see Individualization of Dosage)

Individualization of Dosage

Physicians should individualize treatment using a progressive plan of pain management such as outlined by the World Health Organization, the American Pain Society and the Federation of State Medical Boards Model Guidelines. Healthcare professionals should follow appropriate pain management principles of careful assessment and ongoing monitoring. AVINZA (morphine sulfate) is on the third step of the WHO three step analgesic ladder and is of most benefit when a constant level of opioid analgesia is used as a platform from which break-through pain is managed. Once acceptable pain relief is no longer achieved from combinations of non-opioid medications (NSAIDs and acetaminophen) and intermittent usage of moderate or strong opioids, conversion to a 24-hour oral morphine equivalent is warranted.

The dose may be titrated as frequently as every other day to control analgesia. In the event that break-through pain occurs, AVINZA may be supplemented with a small dose (5-15% of the total daily dose of morphine) of a short-acting analgesic.

When AVINZA is chosen as the initial opioid for patients who do not have a proven tolerance to opioids, patients should be treated initially at a dose of 30 mg once-daily (at 24-hour intervals). For opioid-naïve patients, the dose should be increased conservatively. For such patients, it is recommended that the dose of AVINZA be adjusted in increments not greater than 30 mg every 4 days. Some degree of tolerance may occur, requiring dosage adjustment until the achievement of a balance between analgesia and opioid side effects. When necessary, the total dose of AVINZA should be increased until pain relief is reached or clinically significant opioid-related adverse reactions occur.

Alternative Methods of Administration

AVINZA beads sprinkled over applesauce were found to be bioequivalent to AVINZA capsules swallowed whole under fasting conditions in a study of healthy volunteers. Absorption of the beads sprinkled on other foods has not been tested. This method of administration may be beneficial for patients who have difficulty swallowing whole capsules or tablets.

1. Sprinkle the entire contents of the capsule(s) onto a small amount of applesauce. The applesauce should be at room temperature or cooler. Use immediately. (see also CLINICAL PHARMACOLOGY, Food Effects)
2. Swallow mixture without chewing or crushing beads.
3. Rinse mouth and swallow to ensure all beads have been ingested.
4. Patients should consume the entire portion and should not divide applesauce into separate doses.

Conversion from AVINZA to Other Pain Control Therapies

It is important to remember that the persistence of AVINZA-derived plasma morphine concentrations may be in excess of 36 hours when making a conversion to other pain control therapies.

Conversion from AVINZA to Other Controlled-Release Oral Morphine Formulations

For a given dose, the same total amount of morphine is available from AVINZA as from oral morphine solution or controlled-release morphine tablets. The extended duration of release of morphine from AVINZA results in reduced maximum and increased minimum plasma morphine concentrations than with shorter acting morphine products. Conversion from AVINZA to the same total daily dose of another controlled-release morphine formulation could lead to either excessive sedation at peak serum levels or inadequate analgesia at trough serum levels. Dosage adjustment with close observation is recommended.

Conversion from AVINZA to Parenteral Opioids

When converting from AVINZA to parenteral opioids, it is best to calculate an equivalent parenteral dose and then initiate treatment at half of this calculated value. As an example, an estimated total 24-hour parenteral morphine requirement of a patient receiving AVINZA is one-third of the dose of AVINZA. This is because the oral bioavailability of morphine is one-third that of parenteral morphine. This estimated dose should then be divided in half, and this last calculated dose is the total daily dose. This value should be further divided by six if the desire is to dose with parenteral morphine every four hours.

Consider a patient taking 360 mg of AVINZA daily. First, divide by 3, to account for differences in bioavailability between oral and parenteral morphine. This new figure, 120 mg, is the estimated total 24-hour requirement of parenteral morphine. Dividing by 2, the result gives the total daily dose of 60 mg. If it is decided to administer the drug at four-hour intervals, then administer 10 mg (60 divided by 6) every four hours.

Although this approach may require a dosage increase in the first 24 hours for many patients, this method is recommended, as it is less likely to result in overdose. Overdose is more likely to occur when administering an equivalent dose of parenteral morphine without titration. Provision for break-through pain should be made.

Cessation of Therapy

When the patient no longer requires therapy with AVINZA capsules, doses should be tapered gradually to prevent signs and symptoms of withdrawal in the physically dependent patient.

SAFETY AND HANDLING

AVINZA consists of hard gelatin capsules containing polymer-coated morphine sulfate beads that pose no known risk of handling to healthcare workers. All opioids are liable to diversion and misuse both by the general public and healthcare workers and should be handled accordingly.

HOW SUPPLIED

30 mg Capsule: size 3 capsule, yellow cap imprinted AVINZA and white, opaque body imprinted 30 mg and 505.

NDC 60793-605-01: Bottles of 100 capsules.

45 mg Capsule: size 3 capsule, light blue cap imprinted AVINZA and white, opaque body imprinted 45 mg and 509.

NDC 60793-603-01: Bottles of 100 capsules.

60 mg Capsule: size 3 capsule, bluish-green cap imprinted AVINZA and white, opaque body imprinted 60 mg and 506.

NDC 60793-606-01: Bottles of 100 capsules.

75 mg Capsule: size 1 capsule, orange cap imprinted AVINZA and white, opaque body imprinted 75 mg and 510.

NDC 60793-604-01: Bottles of 100 capsules.

90 mg Capsule: size 1 capsule, red cap imprinted AVINZA and white, opaque body imprinted 90 mg and 507.

NDC 60793-607-01: Bottles of 100 capsules.

120 mg Capsule: size 1 capsule, blue-violet cap imprinted AVINZA and white, opaque body imprinted 120 mg and 508.

NDC 60793-608-01: Bottles of 100 capsules.

Store at 25°C (77°F); excursions permitted to 15-30°C (59-86°F). [see USP Controlled Room Temperature]

Protect from light and moisture.

Dispense in a tight, light-resistant container as defined in USP.

CAUTION: DEA Order Form Required.

Rx Only.

Prescribing Information as of April 2008.

Manufactured for:
King Pharmaceuticals, Inc.
Bristol, TN 37620

AVINZA® Information Service: 1-800-776-3637

Utilizing technology developed by:
Elan Pharma International, Ltd.,
Monksland, Athlone
Co Westmeath, Ireland

AVINZA® is a registered trademark of King Pharmaceuticals Research and Development, Inc.

SODAS® is a registered trademark of Elan Pharma International, Ltd.,

U.S. Patent No.: 6,066,339